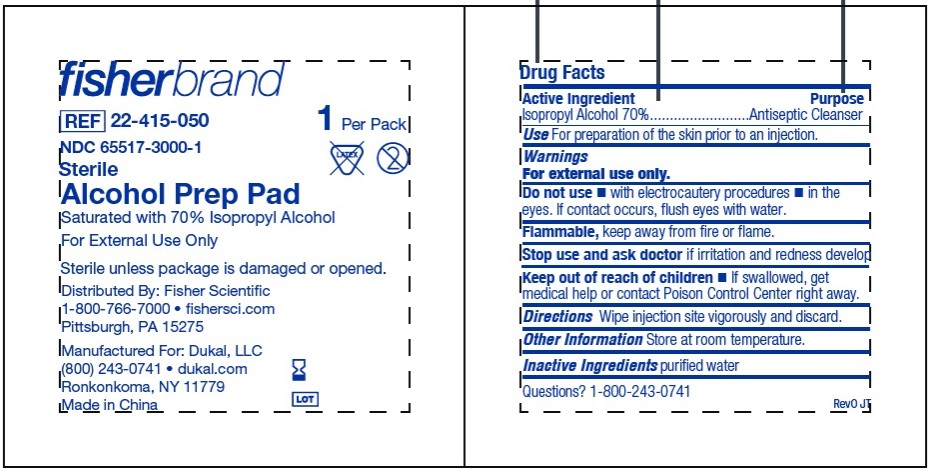 DRUG LABEL: Dukal/Fisher Alcohol Prep Pad
NDC: 65517-3000 | Form: SWAB
Manufacturer: Dukal LLC
Category: otc | Type: HUMAN OTC DRUG LABEL
Date: 20251212

ACTIVE INGREDIENTS: ISOPROPYL ALCOHOL 0.7 mL/1 mL
INACTIVE INGREDIENTS: WATER

65517-3000-1 - Alcohol Prep Pad

Active Ingredient

Isopropyl Alcohol 70%

Purpose

Antiseptic Cleanser

Use

For preparation of the skin prior to an injection

Warnings

- For external use only
- Flammable, Keep awy from fire or flame

Do not use

- with electrocautery procedures
- in the eyes. If contact occurs, flush eyes with water.

Stop use and ask doctor if irritation and redness develop.

Keep out of reach of children

- If swallowed, get medical help or contact Poison Control Center right away.

Directions

Wipe injection site vigorously and discard.

OTHER SAFETY INFORMATION

Store at room temperature.

INACTIVE INGREDIENT

purified water

PACKAGE LABEL

fisher REF 22-415-050

healthcare NDC 65517-3000-1

1 Per Pack

Sterile

Alcohol Prep Pad

Saturated with 70% Isopropyl Alcohol

For External Use Only

Sterile unless package is damaged or opened.

Distributed by: Fisher Healthcare

1-800-766-7000 - fishersci.com

Pittsburgh, PA 15275

Manufactured For: Dukal, LLC

(800) 243-0741 - dukal.com

Ronkonkoma, NY 11779

Made in China